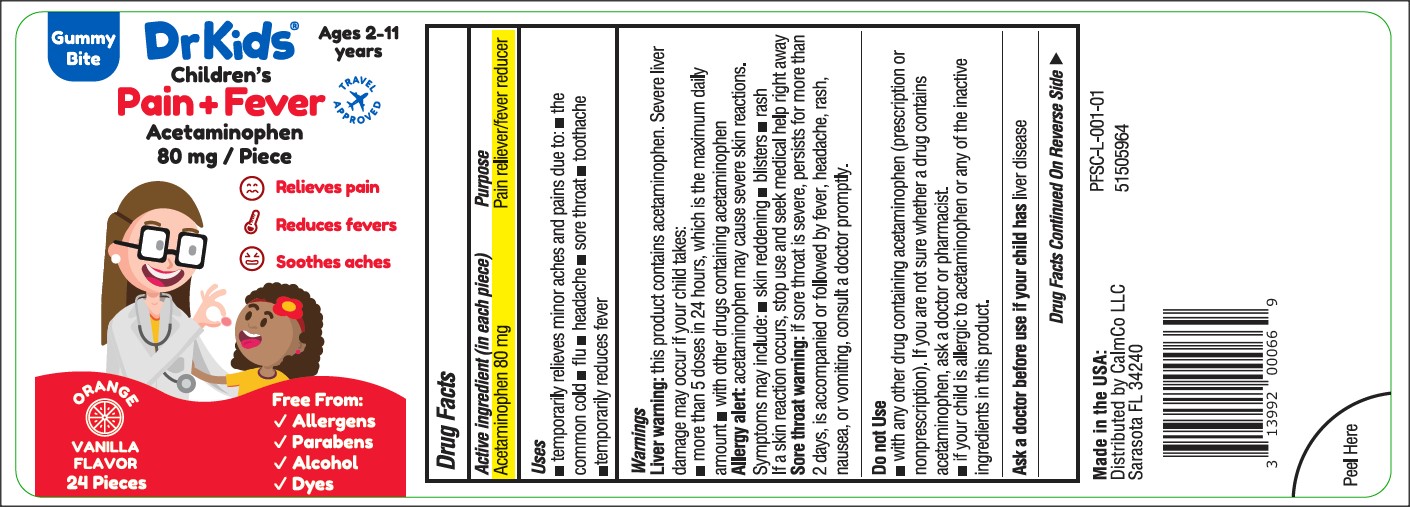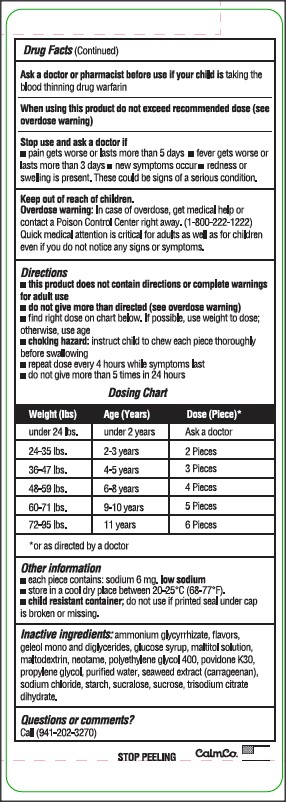 DRUG LABEL: DrKids Childrens Pain and Fever
NDC: 73282-2480 | Form: BAR, CHEWABLE
Manufacturer: CalmCo LLC
Category: otc | Type: HUMAN OTC DRUG LABEL
Date: 20241207

ACTIVE INGREDIENTS: ACETAMINOPHEN 80 mg/1 1
INACTIVE INGREDIENTS: AMMONIUM GLYCYRRHIZATE; GLYCERYL MONO AND DIPALMITOSTEARATE; MALTITOL; POLYETHYLENE GLYCOL 400; NEOTAME; STARCH, CORN; PROPYLENE GLYCOL; WATER; CARRAGEENAN; SUCROSE; SUCRALOSE; CORN SYRUP; SODIUM CHLORIDE; TRISODIUM CITRATE DIHYDRATE; POVIDONE K30; MALTODEXTRIN

DrKids Children's Pain and Fever (USP)

Active ingredient and Purpose

Active Ingredient (in each piece) | Purpose
Acetaminophen 80mg .......................... | Pain reliever/ fever reducer

Uses

Temporarily relieves minor aches and pains due to:

- the common cold
- flu
- headache
- sore throat
- toothache
- temporarily reduces fever

Warnings

Liver warning:this product contains acetaminophen. Severe liver damage may occur if your child takes

- more than 5 doses in 24 hours, which is the maximum daily amount
- with other drugs containing acetaminophen

Allergy alert:acetaminophen may cause severe skin reactions. Symptoms may include:

- skin reddening
- blisters
- rash

If a skin reaction occurs, stop use and seek medical help right away

Sore throat warning:if sore throat is severe, persists for more than 2 days, is accompanied or followed by fever, headache, rash, nausea, or vomiting, consult a doctor promptly.

Do not use

- with any other drug containing acetaminophen (prescription or nonprescription). If you are not sure whether a drug contains acetaminophen, ask a doctor or pharmacist.
- if your child is allergic to acetaminophen or any of the inactive ingredients in this product.

Ask a doctor before use if your child has

liver disease

Ask a doctor or pharmacist before use if your child is

taking the blood thinning drug warfarin.

When using this product

do not exceed recommended dose (see overdose warning)

Stop use and ask a doctor if

- pain gets worse or lasts more than 5 days
- fever gets worse or lasts more than 3 days
- new symptoms occur
- redness or swelling is present. These could be signs of a serious condition.

Keep out of reach of children.

Overdose warning: In case of overdose, get medical help or contact a Poison Control Center right away. (1-800-222-12220 Quick medical attention is critical for adults as well as for children even if you do not notice any signs or symptoms.

Other Information

- each piece contains: sodium 6 mg. low sodium
- store in a cool dry place between 20-25°C (68-77°F).
- Child Resistant Container; do not use if printed seal under cap is broken or missing.

Inactive Ingredients

ammonium glycyrrhizate, flavors, geleol mono and diglycerides, glucode syrup, maltitol solution, maltodextrin, neotame, polyethylene glycol 400, povidone K30, propylene glycol, purified water, seaweed extract (carrageenan), sodium chloride, starch, sucralose, sucrose, trisodium citrate dihydrate.

Questions or comments?

Call 1-941-202-3270

Directions

- this product does not contain directions or complete warnings for adult use
- do not give more than directed (see overdose warning)
- find right dose on the chart below. If possible, use weight to dose; otherwise, use age
- chocking hazard: instruct child to chew each piece thoroughly before swallowing
- repeat dose every 4 hours while symptoms last
- do not give more than 5 times in 24 hours

Dosing Chart

Weight (lbs) | Age (Years) | Dose (per piece)*
under 24 | under 2 years | ask a doctor
24-35 | 2-3 | 2
36-47 | 4-5 | 3
48-59 | 6-8 | 4
60-71 | 9-10 | 5
72-95 | 11 | 6

*or as directed by a doctor